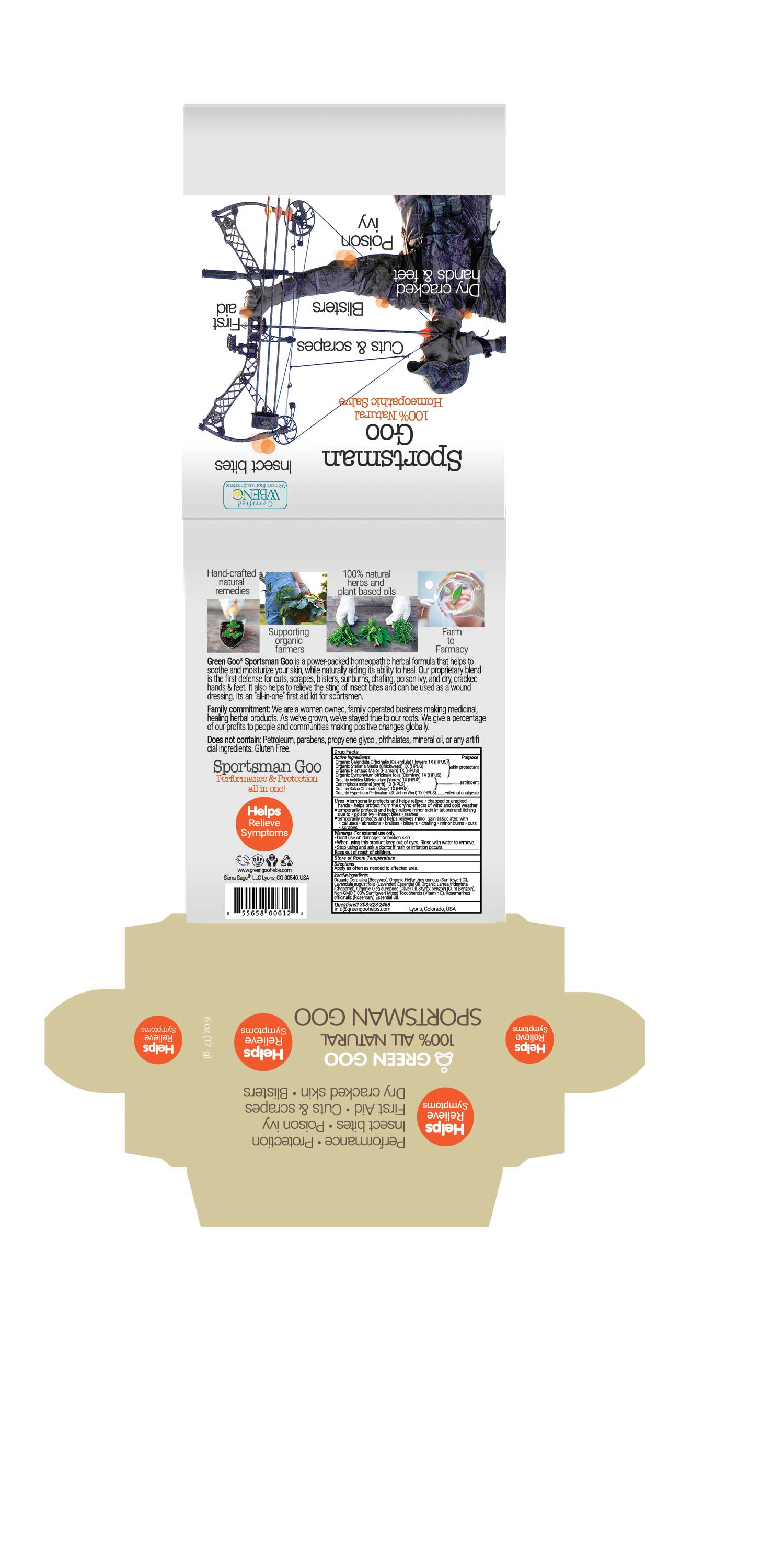 DRUG LABEL: Sportsman Goo
NDC: 70994-605 | Form: SALVE
Manufacturer: Sierra Sage Herbs LLC
Category: homeopathic | Type: HUMAN OTC DRUG LABEL
Date: 20170114

ACTIVE INGREDIENTS: ACHILLEA MILLEFOLIUM FLOWER 1 [hp_X]/17 g; ST. JOHN'S WORT 1 [hp_X]/17 g; STELLARIA MEDIA 1 [hp_X]/17 g; CALENDULA OFFICINALIS FLOWER 1 [hp_X]/17 g; PLANTAGO MAJOR 1 [hp_X]/17 g; COMMIPHORA MYRRHA WHOLE 1 [hp_X]/17 g; SALVIA OFFICINALIS WHOLE 1 [hp_X]/17 g; COMFREY LEAF 1 [hp_X]/17 g
INACTIVE INGREDIENTS: YELLOW WAX; LARREA TRIDENTATA LEAF; ALPHA-TOCOPHEROL; ROSEMARY OIL; STYRAX BENZOIN RESIN; LAVENDER OIL; OLIVE OIL

Sportsman Goo

Purpose Section

Skin Protectant

Astringent

External Analgesic

Active Ingredients

Organic Calendula Officinalis (Calendula) Flowers 1X (HPUS)
Organic Stellaria Media (Chickweed) 1X (HPUS)
Organic Plantago Major (Plantain) 1X (HPUS)
Organic Symphytum officinale folia (Comfrey) 1X (HPUS)

Organic Achillea Millefofolium (Yarrow) 1X (HPUS)
Commiphora molmol (myrrh) 1X (HPUS)
Organic Salvia Officinalis (Sage) 1X (HPUS)
Organic Hypericum Perforatum (St. Johns Wort) 1X (HPUS)

Indications & Usage

• temporarily protects and helps relieve • chapped or cracked hands • helps protect from the drying effects of wind and cold weather
• temporarily protects and helps relieve minor skin irritations and itching due to • poison ivy • insect bites • rashes
• temporarily protects and helps relieves minor pain associated with • calluses • abrasions • bruises • blisters • chafing • minor burns

• cuts • scrapes

Keep out of reach of children section

Keep out of reach of children.

Warnings Section

Warnings For external use only.

• Don’t use on damaged or broken skin.
• When using this product keep out of eyes. Rinse with water to remove.

• Stop using and ask a doctor if rash or irritation occurs.

Storage

Store at room temperature.

Dosage & Administration Section

Apply as often as needed to affected area.

Inactive Ingredients

Organic Cera alba (Beeswax), Organic Helianthus annuus (Sunflower) Oil, Organic Larrea tridentata (Chaparral), Lavandula augustifolia (Lavender) Essential Oil, Organic Olea europaea (Olive) Oil, Rosemarinus officinalis (Rosemary) Essential Oil, Styrax benzoin (Gum Benzoin), Non-GMO (100% Sunflower) Mixed Tocopherols (Vitamin E),